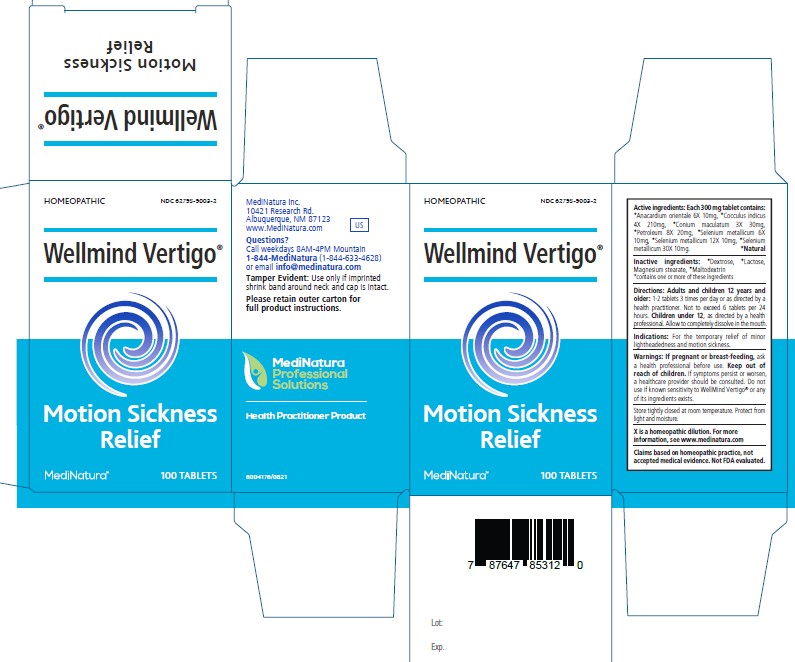 DRUG LABEL: WellMind Vertigo
NDC: 62795-9003 | Form: TABLET
Manufacturer: MediNatura Inc.
Category: homeopathic | Type: HUMAN OTC DRUG LABEL
Date: 20230419

ACTIVE INGREDIENTS: SEMECARPUS ANACARDIUM JUICE 6 [hp_X]/1 1; ANAMIRTA COCCULUS SEED 4 [hp_X]/1 1; CONIUM MACULATUM FLOWERING TOP 3 [hp_X]/1 1; PETROLEUM ALKYLATE 8 [hp_X]/1 1; SELENIUM 6 [hp_X]/1 1
INACTIVE INGREDIENTS: LACTOSE MONOHYDRATE; MAGNESIUM STEARATE; DEXTROSE; MALTODEXTRIN

WellMind Vertigo

Warnings:

If pregnant or breast-feeding, ask
a health professional before use. Keep out of
reach of children. If symptoms persist or worsen,
a healthcare provider should be consulted. Do not
use if known sensitivity to WellMind Vertigo® or any
of its ingredients exists.

Active ingredients

Each 300 mg tablet contains:
*Anacardium orientale 6X 10mg, *Cocculus indicus
4X 210mg, *Conium maculatum 3X 30mg,
*Petroleum 8X 20mg, *Selenium metallicum 6X
10mg, *Selenium metallicum 12X 10mg, *Selenium
metallicum 30X 10mg. *Natural

Inactive ingredients:

*Dextrose, *Lactose,
Magnesium stearate, *Maltodextrin
*contains one or more of these ingredients

Purpose

Motion Sickness
Relief

Directions:

Adults and children 12 years and
older: 1-2 tablets 3 times per day or as directed by a
health practitioner. Not to exceed 6 tablets per 24
hours. Children under 12, as directed by a health
professional. Allow to completely dissolve in the mouth

Keep out of reach of children

Indications:

For the temporary relief of minor
lightheadedness and motion sickness.